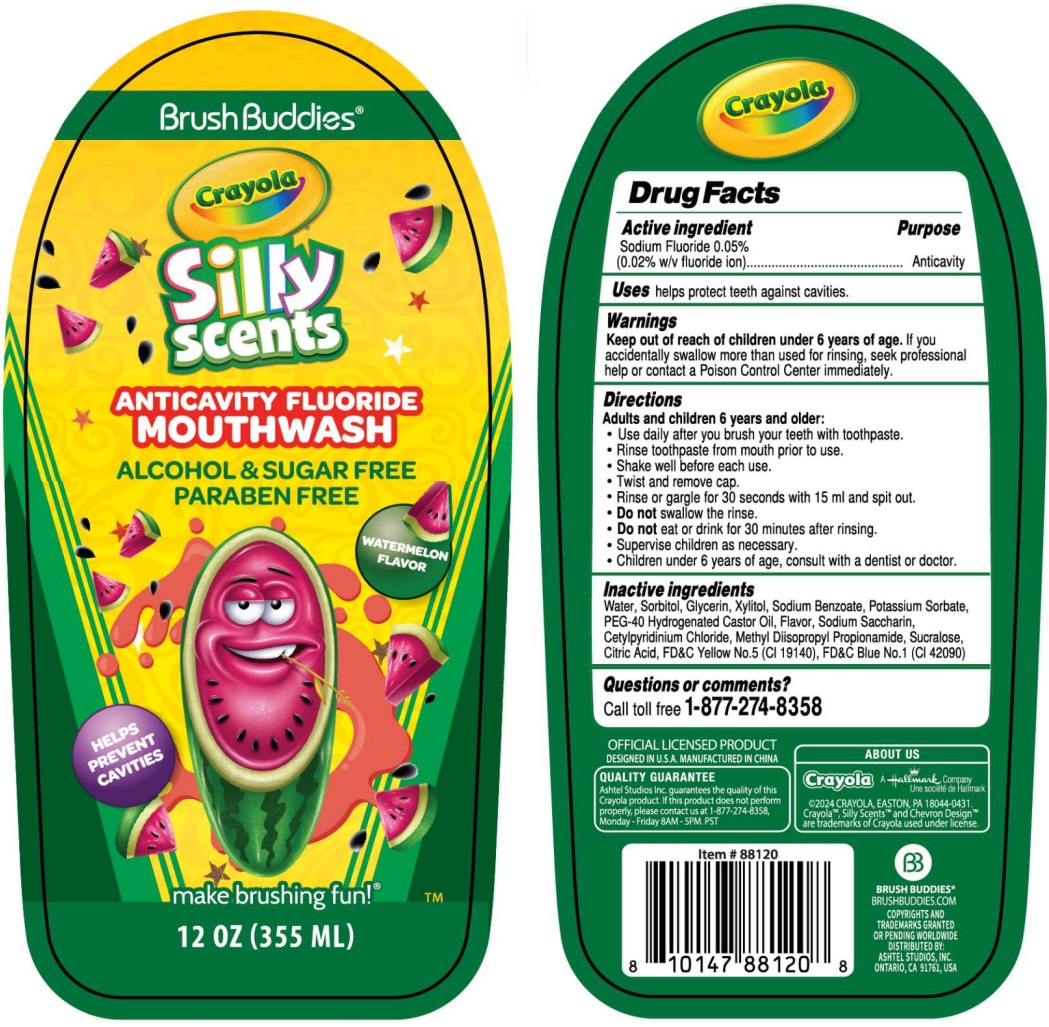 DRUG LABEL: Brush Buddies Crayola ANTICAVITY FLUORIDE - WATERMELON FLAVOR
NDC: 70108-093 | Form: MOUTHWASH
Manufacturer: Ashtel Studios Inc.
Category: otc | Type: HUMAN OTC DRUG LABEL
Date: 20240730

ACTIVE INGREDIENTS: SODIUM FLUORIDE 0.05 g/100 mL
INACTIVE INGREDIENTS: WATER; SORBITOL; GLYCERIN; XYLITOL; SODIUM BENZOATE; POTASSIUM SORBATE; POLYOXYL 40 HYDROGENATED CASTOR OIL; SACCHARIN SODIUM; CETYLPYRIDINIUM CHLORIDE; METHYL DIISOPROPYL PROPIONAMIDE; SUCRALOSE; CITRIC ACID MONOHYDRATE; FD&C YELLOW NO. 5; FD&C BLUE NO. 1

Brush Buddies® Crayola Silly scents ANTICAVITY FLUORIDE MOUTHWASH

Active ingredient

Sodium Fluoride 0.05%
(0.02% w/v fluoride ion)

Purpose

Anticavity

Uses

helps protect teeth against cavities.

Warnings

Keep out of reach of children under 6 years of age. If you accidentally swallow more than used for rinsing, seek professional help or contact a Poison Control Center immediately.

Directions

Adults and children 6 years and older:
• Use daily after you brush your teeth with toothpaste.
• Rinse toothpaste from mouth prior to use.
• Shake well before each use.
• Twist and remove cap.
• Rinse or gargle for 30 seconds with 15 ml and spit out.
• Do not swallow the rinse.
• Do not eat or drink for 30 minutes after rinsing.
• Supervise children as necessary.
• Children under 6 years of age, consult with a dentist or doctor.

Inactive ingredients

Water, Sorbitol, Glycerin, Xylitol, Sodium Benzoate, Potassium Sorbate, PEG-40 Hydrogenated Castor Oil, Flavor, Sodium Saccharin, Cetylpyridinium Chloride, Methyl Diisopropyl Propionamide, Sucralose, Citric Acid, FD&C Yellow No.5 (CI 19140), FD&C Blue No.1 (CI 42090)

Questions or comments?

Call toll free 1-877-274-8358

Silly scents
ALCOHOL & SUGAR FREE
PARABEN FREE
HELPS PREVENT CAVITIES
make brushing fun!®

OFFICIAL LICENSED PRODUCT
DESIGNED IN U.S.A. MANUFACTURED IN CHINA
QUALITY GUARANTEE
Ashtel Studios Inc. guarantees the quality of this Crayola product. If this product does not perform properly, please contact us at 1-877-274-8358, Monday - Friday 8AM - 5PM. PST
ABOUT US
Crayola A Hallmark Company
©2024 CRAYOLA, EASTON, PA 18044-0431.
Crayola™, Silly Scents™ and Chevron Design™ are trademarks of Crayola used under license.
BRUSH BUDDIES®
BRUSHBUDDIES.COM
COPYRIGHTS AND TRADEMARKS GRANTED OR PENDING WORLDWIDE
DISTRIBUTED BY:
ASHTEL STUDIOS, INC.
ONTARIO, CA 91761, USA